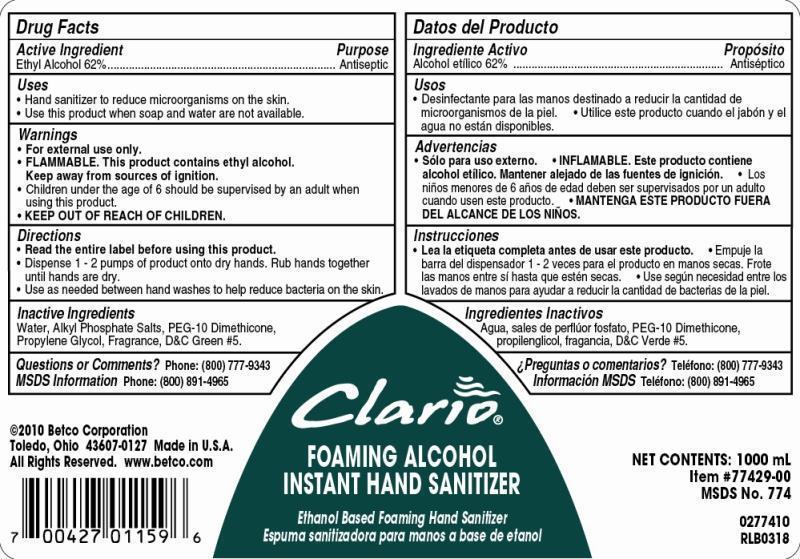 DRUG LABEL: Clario Foaming Alcohol Instant Hand Sanitizer
NDC: 65601-774 | Form: SOAP
Manufacturer: Betco Corporation, Ltd.
Category: otc | Type: HUMAN OTC DRUG LABEL
Date: 20121112

ACTIVE INGREDIENTS: ALCOHOL 0.7 mL/1 mL
INACTIVE INGREDIENTS: WATER; DIETHANOLAMINE; PEG-10 DIMETHICONE (600 CST); PROPYLENE GLYCOL; D&C GREEN NO. 5

Clario Foaming Alcohol Instant Hand Sanitizer

Clario Foaming Alcohol Instant Hand Sanitizer

Active Ingredient

Ethyl Alcohol 62%

Clario Foaming Alcohol Instant Hand Sanitizer

Uses

- Use hand sanitizer to reduce microorganisms on the skin.
- Use this product when soap and water are not available.

Clario Foaming Alcohol Instant Hand Sanitizer

Warnings

- For external use only.
- FLAMMABLE. This product contains ethyl alcohol. Keep away from sources of ignition.
- Children under the age of 6 should be supervised by an adult when using this product.
- Discontinue use is irritation or redness develops.
- KEEP OUT OF REACH OF CHILDREN.

Clario Foaming Alcohol Instant Hand Sanitizer

Directions

- Read the entire label before using this product.
- Dispense 0.8 mL of product onto dry hands. Rub hands together until hands are dry.
- Use as needed between hand washes to help reduce bacteria on the skin.

Clario Foaming Alcohol Instant Hand Sanitizer

Inactive Ingredients

Water, Alkyl Phosphate Salts, PEG-10 Dimethicone, Propylene Glycol, Fragrance, D&C Green #5.

Clario Foaming Alcohol Instant Hand Sanitizer

Questions or Comments? Phone: (800) 777-9343

MDS information:(800) 891-4965

Clario Foaming Alcohol Instant Hand Sanitizer

Purpose

Antiseptic

Clario Foaming Alcohol Instant Hand Sanitizer

KEEP OUT OF REACH OF CHILDREN

Clario Foaming Alcohol Instant Hand Sanitizer

Alcohol Based Foaming Hand Sanitizer

Net Contents: 1000 mL

Item #77429-00

MSDS No. 774

2010 Beto Corporation

Toledo, Ohio 43607-0127 Made in U.S.A.

All Rights Reserved. www.betco.com